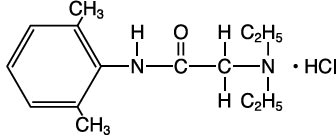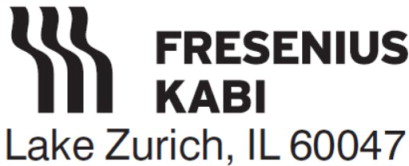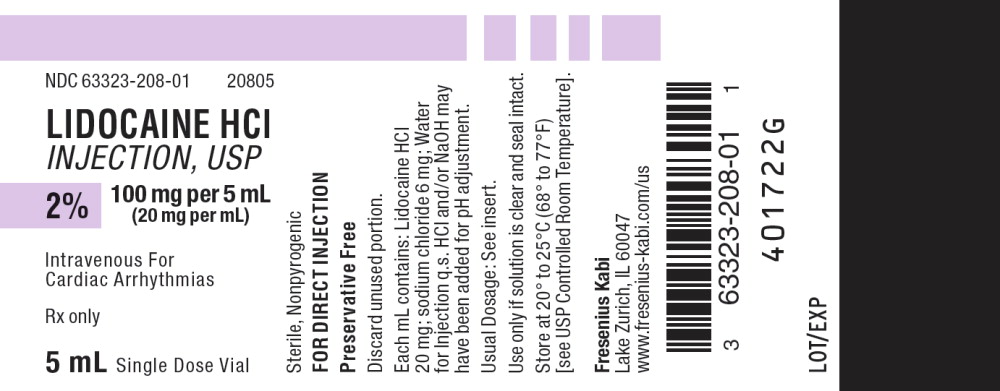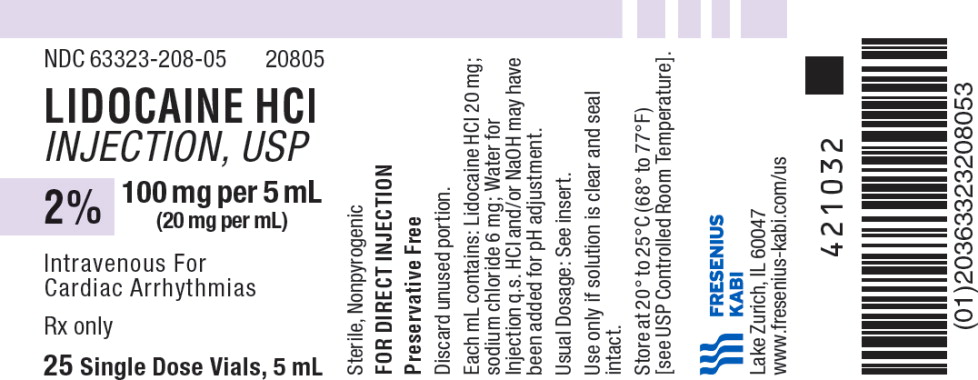 DRUG LABEL: Lidocaine
NDC: 63323-208 | Form: INJECTION, SOLUTION
Manufacturer: Fresenius Kabi USA, LLC
Category: prescription | Type: HUMAN PRESCRIPTION DRUG LABEL
Date: 20250220

ACTIVE INGREDIENTS: LIDOCAINE HYDROCHLORIDE 20 mg/1 mL
INACTIVE INGREDIENTS: SODIUM CHLORIDE 6 mg/1 mL; HYDROCHLORIC ACID; SODIUM HYDROXIDE; WATER

Lidocaine Hydrochloride Injection USP

INTRAVENOUS FOR CARDIAC ARRHYTHMIAS

DESCRIPTION

Lidocaine hydrochloride, chemical name: acetamide, 2-(diethylamino)-N-(2,6-dimethylphenyl)-, monohydrochloride has the following structural formula:

Lidocaine Hydrochloride Injection, USP intravenous for cardiac arrhythmias, is a sterile, nonpyrogenic solution prepared from lidocaine with the aid of hydrochloric acid in Water for Injection.

Each mL contains: Lidocaine HCl 20 mg; Sodium Chloride 6 mg; Water for Injection q.s. Hydrochloric acid and/or sodium hydroxide may have been added for pH adjustment (pH 5.0 to 7.0). The container is for single use; solution contains no preservative.

CLINICAL PHARMACOLOGY

Lidocaine hydrochloride exerts its antiarrhythmic effect by raising the electrical stimulation threshold of the ventricle during diastole. In usual therapeutic doses, lidocaine hydrochloride produces no change in myocardial contractility, systemic arterial pressure or in absolute refractory period.

Onset of action is rapid after an intravenous bolus with a duration of action of approximately 15 to 20 minutes.

Approximately 90% of an administered dose of lidocaine hydrochloride is metabolized in the liver. The remainder (10%) of the drug is excreted unchanged in the urine. Pharmacokinetic data indicate reduced elimination of lidocaine after prolonged (24 hours) infusion with resultant prolongation of the half-life to approximately three times that seen following a single administration.

INDICATIONS AND USAGE

Lidocaine Hydrochloride Injection, USP administered intravenously is specifically indicated in the acute management of 1) ventricular arrhythmias occurring during cardiac manipulation such as cardiac surgery, and 2) life-threatening arrhythmias, particularly those which are ventricular in origin, such as those which occur during acute myocardial infarction.

CONTRAINDICATIONS

Lidocaine Hydrochloride Injection, USP is contraindicated in patients with a known history of hypersensitivity to local anesthetics of the amide type. Lidocaine Hydrochloride Injection, USP should not be used in patients with STOKES-ADAMS syndrome, Wolff-Parkinson-White syndrome, or with severe degrees of sinoatrial, atrioventricular or intraventricular block.

WARNINGS

Constant monitoring of the electrocardiogram and blood pressure is essential in the proper administration of Lidocaine Hydrochloride Injection, USP intravenously. If hypotension or excessive depression of cardiac conductivity (such as prolongation of the PR interval and QRS complex and the appearance of aggravation of arrhythmias) is seen, administration of Lidocaine Hydrochloride Injection, USP should be discontinued.

Emergency resuscitative equipment and drugs must be immediately available to manage possible adverse reactions involving the cardiovascular, respiratory, or central nervous system.

Occasional acceleration of ventricular rate may occur when Lidocaine Hydrochloride Injection, USP is administered to patients with atrial fibrillation.

Toxicity may be manifest as central nervous system depression (sedation) or irritability (twitching), which may progress to frank convulsions accompanied by respiratory depression and/or arrest. Early recognition of premonitory signs, assurance of adequate oxygenation and (where necessary) establishment of artificial airway with ventilatory support are essential to management of the problem. Should convulsions persist despite ventilatory support, small doses of anticonvulsant drugs may be used intravenously. Examples of such drugs include benzodiazepines (e.g., diazepam, lorazepam), or an ultrashort acting barbiturate (e.g., thiopental or thiamylal). If the patient is under anesthesia, a short-acting muscle relaxant (succinylcholine) may be used. Longer acting drugs should be used only when recurrent convulsions are evidenced.

PRECAUTIONS

The safe use of Lidocaine Hydrochloride Injection, USP requires careful ECG observation in an environment equipped and by persons trained for resuscitation.

General

Caution should be employed in the repeated use of Lidocaine Hydrochloride Injection, USP in patients with severe liver or renal disease because accumulation may occur and lead to toxic phenomena since Lidocaine Hydrochloride Injection, USP is metabolized mainly in the liver and excreted by the kidneys. This drug should also be used with caution in patients with hypovolemia and shock and all forms of heart block (see CONTRAINDICATIONS and WARNINGS).

In patients with sinus bradycardia or incomplete heart block, the administration of Lidocaine Hydrochloride Injection, USP intravenously or the elimination of ventricular ectopic beats without prior acceleration in heart rate may promote more frequent and serious ventricular arrhythmias or complete heart block. (See CONTRAINDICATIONS.)

Many potent anesthetic drugs, neuromuscular blocking agents and possibly amide local anesthetics may serve as triggering agents for the fulminant hypermetabolic process termed malignant hyperthermia. Key to successful outcome of fulminant hypermetabolism is early recognition of premonitory signs, i.e., unexplained or unexpected tachycardia and increased metabolic rate as evidenced by respiratory and/or metabolic acidosis. Treatment includes administration of oxygen and discontinuation of lidocaine hydrochloride administration and where necessary administration of dantrolene sodium. For additional information on management, see prescribing information for dantrolene sodium.

Drug Interaction

The effect of Lidocaine Hydrochloride Injection, USP for the management of cardiac arrhythmias is potentiated with the simultaneous or prior administration of propranolol.

Lidocaine Hydrochloride Injection, USP should be used with caution in patients with digitalis toxicity accompanied by atrioventricular block. (See CONTRAINDICATIONS.)

Drug interaction was studied with several beta-blockers (propranolol, metoprolol, nadolol, and pindolol). Pretreatment with propranolol, metoprolol and nadolol increased the serum concentration of lidocaine. Pretreatment with pindolol did not affect the serum concentration of lidocaine.

Carcinogenesis, Mutagenesis, Impairment of Fertility

Studies of Lidocaine Hydrochloride Injection, USP in animals to evaluate the carcinogenic and mutagenic potential or the effect on fertility have not been conducted.

Pregnancy Category B

Reproductive studies have been performed in the rat at doses up to 5 times the human dose and have revealed no evidence of impaired fertility or harm to the fetus due to Lidocaine Hydrochloride Injection, USP. There are, however, no adequate and well controlled studies in pregnant women. Because animal reproduction studies are not always predictive of human response, this drug should be used in pregnancy only if clearly needed.

Labor and Delivery

The effects of Lidocaine Hydrochloride Injection, USP solution on the mother and the fetus, when used in the management of cardiac arrhythmias during labor and delivery, are not known. Lidocaine Hydrochloride Injection, USP readily crosses the placental barrier.

Nursing Mothers

It is not known whether this drug is excreted in human milk. Because many drugs are excreted in human milk, caution should be exercised when Lidocaine Hydrochloride Injection, USP is administered to a nursing woman.

Pediatric Use

Safety and effectiveness in children have not been established by controlled clinical studies. (See DOSAGE AND ADMINISTRATION.)

ADVERSE REACTIONS

To report SUSPECTED ADVERSE REACTIONS, contact Fresenius Kabi USA, LLC at 1-800-551-7176 or FDA at 1-800-FDA-1088 or www.fda.gov/medwatch.

Most adverse reactions accompanying administration of Lidocaine Hydrochloride Injection, USP result from systemic toxicity affecting primarily the central nervous system and the cardiovascular system.

Systemic reactions of the following types have been reported:

1. Central Nervous System

Light-headedness; drowsiness; dizziness; apprehension; euphoria; tinnitus; blurred vision or double vision; vomiting; sensations of heat; cold or numbness; twitching; tremors; convulsions; unconsciousness; respiratory depression and arrest.

2. Cardiovascular System

Hypotension; cardiovascular collapse; and bradycardia which may lead to cardiac arrest. Continuous monitoring of blood pressure and the electrocardiogram are essential to prevent these events.

3. Allergic reactions may occur but are infrequent. There have been no reports of cross-sensitivity between lidocaine hydrochloride and procainamide or between lidocaine and quinidine.

OVERDOSAGE

Management of Adverse Reactions—

1. In the case of severe reaction, discontinue the use of Lidocaine Hydrochloride Injection, USP.
2. Institute emergency resuscitative procedures and administer the emergency drugs necessary to manage the severe reaction. For severe convulsions, small increments of diazepam or an ultra short-acting barbiturate (thiopental or thiamylal); or if those are not available a short-acting barbiturate (pentobarbital or secobarbital); or if the patient is under anesthesia, a short-acting muscle relaxant (succinylcholine) may be given intravenously. Muscle relaxants and intravenous medications should only be used by those familiar with their use. Patency of the airway and adequacy of ventilation must be assured. (See WARNINGS.)
3. Should circulatory depression occur, vasopressors, such as ephedrine, or meta raminol may be used. Should cardiac arrest occur, immediate initiation of standard CPR procedures should commence.

DOSAGE AND ADMINISTRATION

Adult

For Direct Injection–The usual dose is 50 to 100 mg administered intravenously under ECG monitoring. This dose may be administered at the rate of approximately 25 to 50 mg/min. Sufficient time should be allowed to enable a slow circulation to carry the drug to the site of action. If the initial injection of 50 to 100 mg does not produce a desired response, a second dose may be repeated after 5 minutes.

NO MORE THAN 200 TO 300 MG OF LIDOCAINE HYDROCHLORIDE INJECTION, USP SHOULD BE ADMINISTERED DURING A ONE HOUR PERIOD.

This product is for DIRECT INJECTION ONLY. For continuous infusion protocol, see prescribing information for lidocaine hydrochloride, USP for infusion solution.

Pediatric

Although controlled clinical studies to establish pediatric dosing schedules have not been conducted, the American Heart Association’s Standards and Guidelines recommends a bolus dose of 1 mg/kg followed by an infusion rate of 30 mcg/kg/min.

This product is for DIRECT INJECTION ONLY. For continuous infusion protocol, see prescribing information for lidocaine hydrochloride, USP for infusion solution.

Sterilization, Storage and Technical Procedures

It is recommended that chemical disinfection be accomplished by wiping the vial thoroughly with cotton or gauze that has been moistened with either 91% isopropyl alcohol or 70% ethyl alcohol, just prior to use. Store at 20° to 25°C (68° to 77°F) [see USP Controlled Room Temperature].

Parenteral drug products should be inspected visually for particulate matter and discoloration prior to administration, whenever solution and container permit.

HOW SUPPLIED:

For Direct Injection Only

Lidocaine Hydrochloride Injection, USP

Product Code | Unit of Sale | Strength | Each
20805 | NDC 63323-208-05 Unit of 25 | 2% 100 mg per 5 mL (20 mg per mL) | NDC 63323-208-01 5 mL Single Dose Vial

Preservative Free

Discard Unused Portion.

Use only if solution is clear and seal intact.

www.fresenius-kabi.com/us

45775D

Revised: May 2022

PACKAGE LABEL

PACKAGE LABEL - PRINCIPAL DISPLAY – Lidocaine HCl 5 mL Single Dose Vial Label

NDC 63323-208-01 20805

LIDOCAINE HCl

INJECTION, USP

2%

100 mg per 5 mL

(20 mg per mL)

Intravenous For

Cardiac Arrhythmias

Rx only

5 mL Single Dose Vial

PACKAGE LABEL

PACKAGE LABEL - PRINCIPAL DISPLAY – Lidocaine HCl 5 mL Vial Tray Label

NDC 63323-208-05 20805

LIDOCAINE HCl

INJECTION, USP

2%

100 mg per 5 mL

(20 mg per mL)

Intravenous For

Cardiac Arrhythmias

Rx only

25 Single Dose Vials, 5 mL